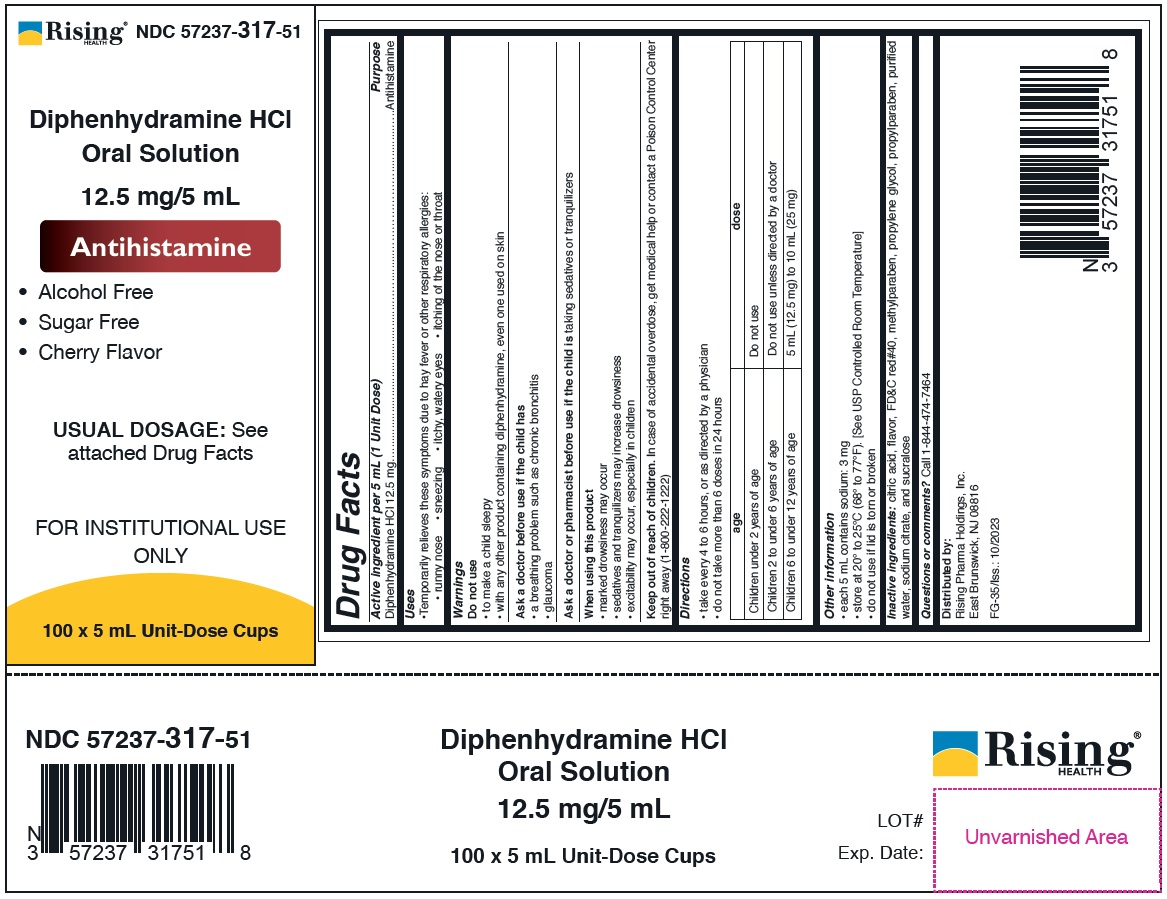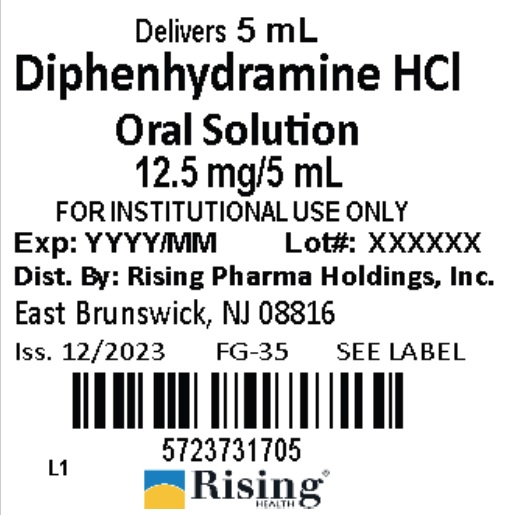 DRUG LABEL: Diphenhydramine HCl Oral Solution
NDC: 57237-317 | Form: SOLUTION
Manufacturer: Rising Pharma Holdings, Inc.
Category: otc | Type: HUMAN OTC DRUG LABEL
Date: 20250701

ACTIVE INGREDIENTS: DIPHENHYDRAMINE HYDROCHLORIDE 12.5 mg/5 mL
INACTIVE INGREDIENTS: CITRIC ACID MONOHYDRATE; FD&C RED NO. 40; METHYLPARABEN; PROPYLENE GLYCOL; PROPYLPARABEN; SODIUM CITRATE; SUCRALOSE; WATER

Diphenhydramine HCl Oral Solution 12.5 mg/5 mL

Drug Facts

Active ingredient per 5 mL (1 Unit Dose)

Diphenhydramine HCl 12.5 mg

Purpose

Antihistamine

Uses

• Temporarily relieves these symptoms due to hay fever or other respiratory allergies:

• runny nose • sneezing • itchy, watery eyes • itching of the nose or throat

Warnings

Do not use

• to make a child sleepy
• with any other product containing diphenhydramine, even one used on skin

Ask a doctor before use if the child has

• a breathing problem such as chronic bronchitis
• glaucoma

Ask a doctor or pharmacist before use if the child is taking sedatives or tranquilizers

When using this product

• marked drowsiness may occur
• sedatives and tranquilizers may increase drowsiness
• excitability may occur, especially in children

Keep out of reach of children. In case of accidental overdose, get medical help or contact a Poison Control Center right away (1-800-222-1222)

Directions

• take every 4 to 6 hours, or as directed by a physician
• do not take more than 6 doses in 24 hours

age | dose
Children under 2 years of age | Do not use
Children 2 to under 6 years of age | Do not use unless directed by a doctor
Children 6 to under 12 years of age | 5 mL (12.5 mg) to 10 mL (25 mg)

Other information

• each 5 mL contains sodium: 3 mg
• store at 20° to 25°C (68° to 77°F). [See USP Controlled Room Temperature]
• do not use if lid is torn or broken

INACTIVE INGREDIENT

Inactive ingredients: citric acid, flavor, FD&C red#40, methylparaben, propylene glycol, propylparaben, purified water, sodium citrate, and sucralose

Questions or comments? Call 1-844-474-7464

Distributed by:
Rising Pharma Holdings, Inc.
East Brunswick, NJ 08816

FG-35/Iss.: 10/2023

NDC Information -

12.5 mg/5 mL

Each 5 mL of Diphenhydramine HCl Oral Solution contains Diphenhydramine HCl 12.5 mg and is supplied in the following oral dosage forms:

NDC 57237-317-05: 5 mL unit dose cup

NDC 57237-317-51: 100 x 5 mL Unit-Dose Cups

PRINCIPAL DISPLAY PANEL

12.5 mg/5 mL

Case Label NDC 57237-317-51

Lid Label NDC 57237-317-05